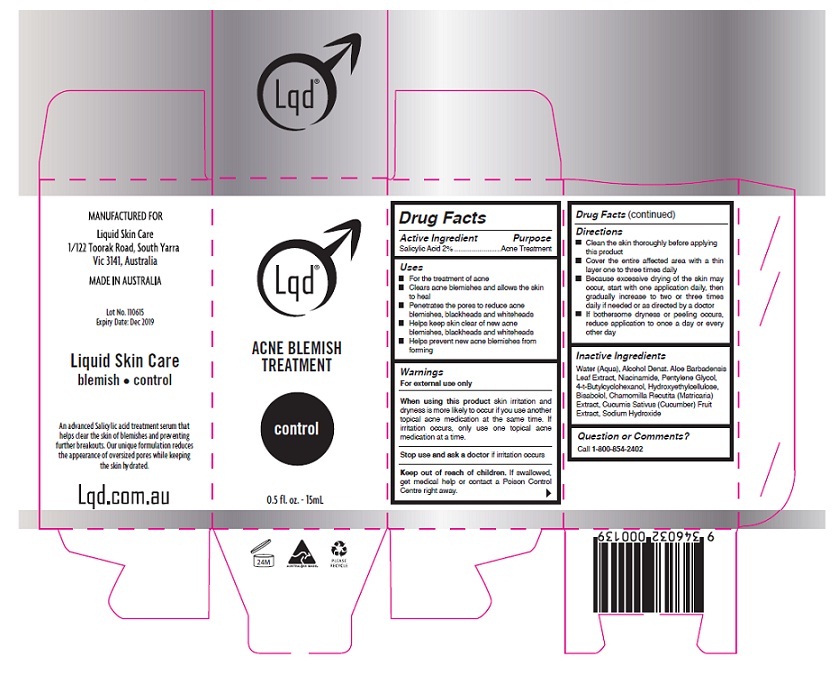 DRUG LABEL: Lqd ACNE BLEMISH TREATMENT control
NDC: 70791-001 | Form: LOTION
Manufacturer: AMAC ENTERPRISES PROPRIETARY LIMITED
Category: otc | Type: HUMAN OTC DRUG LABEL
Date: 20160730

ACTIVE INGREDIENTS: SALICYLIC ACID 2 g/100 mL
INACTIVE INGREDIENTS: WATER; ALCOHOL; ALOE VERA LEAF; NIACINAMIDE; PENTYLENE GLYCOL; 4-TERT-BUTYLCYCLOHEXANOL; HYDROXYETHYL CELLULOSE (5000 MPA.S AT 1%); LEVOMENOL; CHAMOMILE; CUCUMBER; SODIUM HYDROXIDE

Lqd ACNE BLEMISH TREATMENT control

Active Ingredient

Salicylic acid 2%

Purpose

Acne Treatment

Uses

- For the treatment of acne
- Clears acne blemishes and allows the skin to heal
- Penetrates the pores to reduce acne blemishes, blackheads and whiteheads
- Helps keep skin clear of new acne blemishes, blackheads and whiteheads
- Helps prevent new acne blemishes from forming

Warnings

For external use only

When using this product skin irritation and dryness is more likely to occur if you use another topical acne medication at the same time. If irritation occurs, only use one topical acne medication at a time.

Stop use and ask a doctor if irritation occurs

Keep out of reach of children. If swallowed, get medical help or contact a Poison Control Centre right away.

Directions

- Clean the skin thoroughly before applying this product
- Cover the entire affected area with a thin layer one to three times daily
- Because excessive drying of the skin may occur, start with one application daily, then gradually increase to two or three times daily if needed or as directed by a doctor
- If bothersome dryness or peeling occurs, reduce application to once a day or every other day

Inactive Ingredients

Water (Aqua), Alcohol Denat. Aloe Barbadensis Leaf Extract, Niacinamide, Pentylene Glycol, 4-t-Butylcyclohexanol, Hydroxyethylcellulose, Bisabolol, Chamomilla Recutita (Matricaria) Extract, Cucumis Sativus (Cucumber) Fruit Extract, Sodium Hydroxide

Question or Comments?

Call 1-800-854-2402

MANUFACTURED FOR
Liquid Skin Care
1/122 Toorak Road, South Yarra
Vic 3141, Australia

MADE IN AUSTRALIA

An advanced Salicylic acid treatment serum that helps clear the skin of blemishes and preventing further breakouts. Our unique formulation reduces the appearance of oversized pores while keeping the skin hydrated.